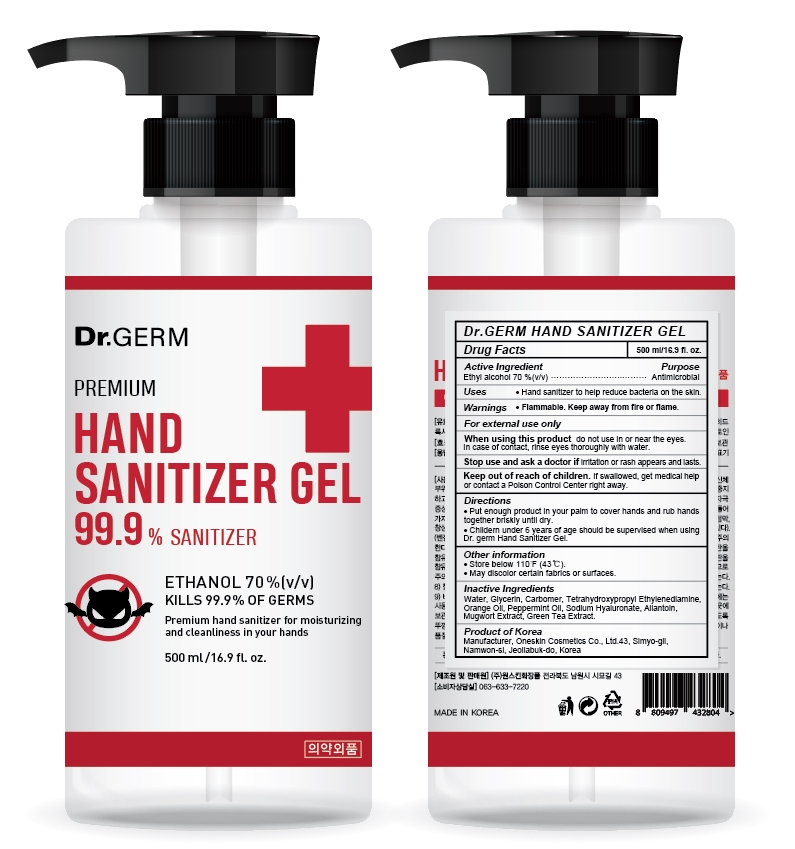 DRUG LABEL: Dr.germ Hand Sanitizer Gel
NDC: 70889-500 | Form: GEL
Manufacturer: Oneskin Cosmetics Co., Ltd.
Category: otc | Type: HUMAN OTC DRUG LABEL
Date: 20200407

ACTIVE INGREDIENTS: ALCOHOL 0.7 mL/1 mL
INACTIVE INGREDIENTS: GLYCERIN; CARBOMER 940; EDETOL; ORANGE OIL; PEPPERMINT OIL; HYALURONATE SODIUM; ALLANTOIN; ARTEMISIA PRINCEPS LEAF; GREEN TEA LEAF; WATER

WARNINGS

Flammable. Keep away from fire or flame.

For external use only

When using this product do not use in or near the eyes.

In case of contact, rinse eyes thoroughly with water.

Stop use and ask a doctor if irritation or rash appears and lasts.

Keep out of reach of children. If swallowed, get medical help or contact a Poision Control Center right away.

ACTIVE INGREDIENT

Ethyl Alcohol 70%

PURPOSE

Antimicrobial

INDICATIONS AND USAGE

- Hand sanitizer to help reduce bacteria on the skin.

INACTIVE INGREDIENT

Water, Glycerin, Carbomer, Tetrahydroxypropyl Ethylenediamine, Orange Oil, Peppermint Oil, Sodium Hyaluronate, Allantoin, Mugwort Extract, Green Tea Extract.

DOSAGE AND ADMINISTRATION

Put enough product in your palm to cover hands and rub hands together briskly until dry.

Childern under 6 years of age should be supervised when using Dr. germ Hand Sanitizer.

STORAGE AND HANDLING

Store below 110oF (43oC).
May discolor certain fabrics or surfaces.

PACKAGE LABEL

Dr.germ Hand Sanitizer Gel